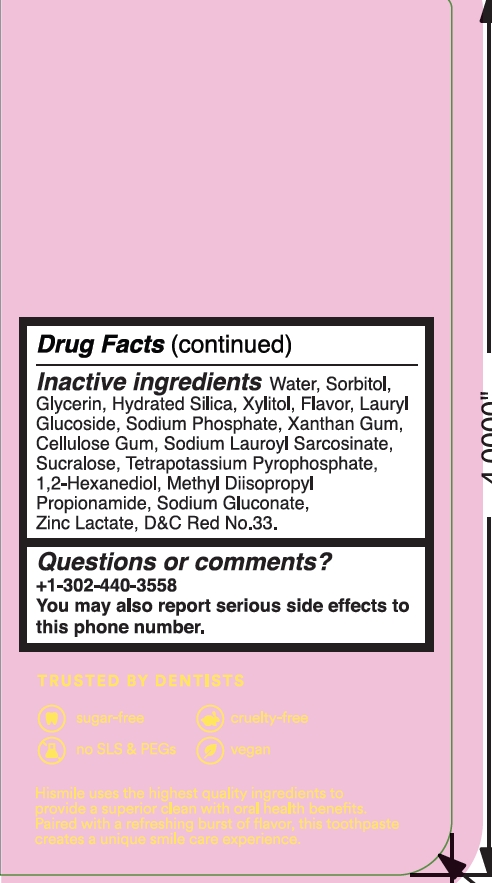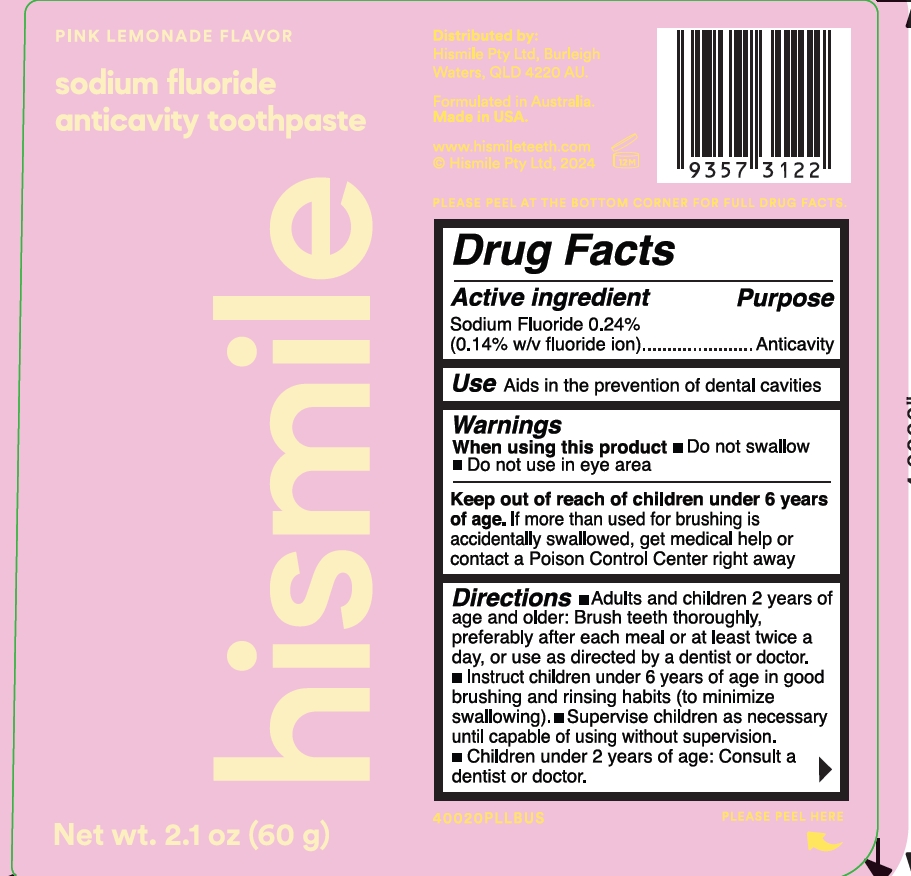 DRUG LABEL: Hismile Pink Lemonade Sodium Fluoride Anticavity Toothpast
NDC: 83013-332 | Form: GEL
Manufacturer: Hismile Pty Ltd
Category: otc | Type: HUMAN OTC DRUG LABEL
Date: 20250313

ACTIVE INGREDIENTS: SODIUM FLUORIDE 0.243 g/100 g
INACTIVE INGREDIENTS: WATER; SORBITOL; XYLITOL; LAURYL GLUCOSIDE; SODIUM PHOSPHATE; XANTHAN GUM; CELLULOSE GUM; POTASSIUM PYROPHOSPHATE; 1,2-HEXANEDIOL; METHYL DIISOPROPYL PROPIONAMIDE; SODIUM GLUCONATE; ZINC LACTATE; GLYCERIN; D&C RED NO. 33; SODIUM LAUROYL SARCOSINATE; HYDRATED SILICA; SUCRALOSE

Hismile Pink Lemonade Sodium Fluoride Anticavity Toothpaste

Active ingredient

sodium fluoride 0.24%

(0.14 w/v fluoride ion)

Purpose

Anticavity

Use

Aids in the prevention of dental cavities.

Warnings

When using this product

Do not swallow

Do not use in eye area

Keep out of reach of children under 6 years of age

If more than used for brushing is accidentally swallowed, get medical help or contact a Poison Control Center right away

Directions

- Adults and children 2 years of age and older: Brush teeth thoroughly, preferably after each meal or at least twice a day, or use as directed by a dentist or doctor.
- Instruct children under 6 years of age in good brushing and rinsing habits (to minimize swallowing).
- Supervise children as necessary until capable of using without supervision.
- Children under 2 years of age: Consult a dentist or doctor.

Inactive ingredients

Water

Sorbitol

Glycerin

Hydrated Silica

Xylitol

Lauryl Glucoside

Sodium Phosphate

Xanthan Gum

Cellulose Gum

Sodium Lauroyl Sarcosinate

Sucralose

Tetrapotassium Pyrophosphate

1,2-Hexanediol

Methyl Diisopropyl Propionamide

Sodium Gluconate

Zinc Lactate

D&C Red No.33